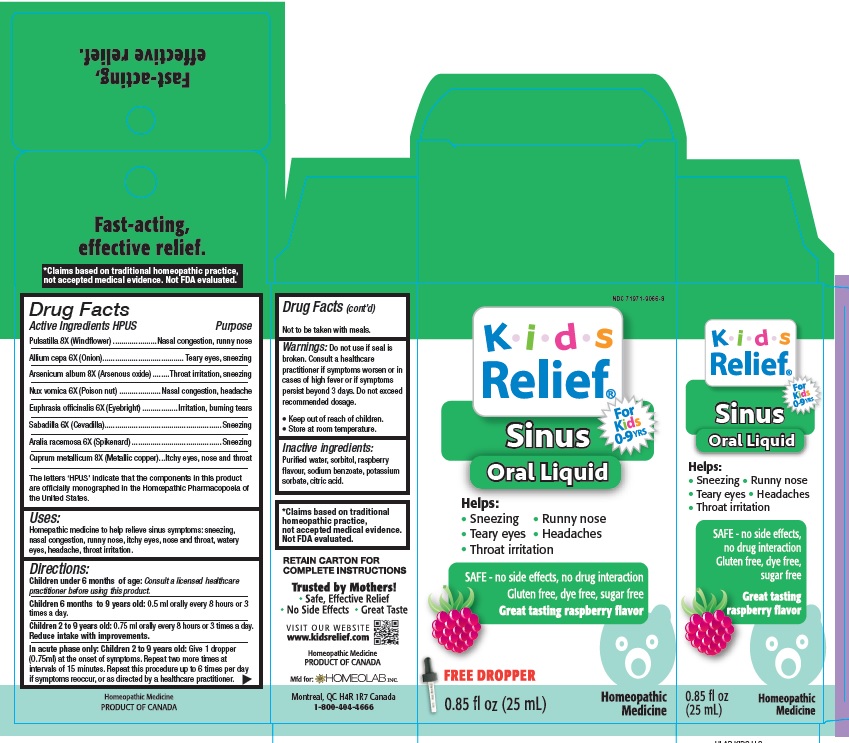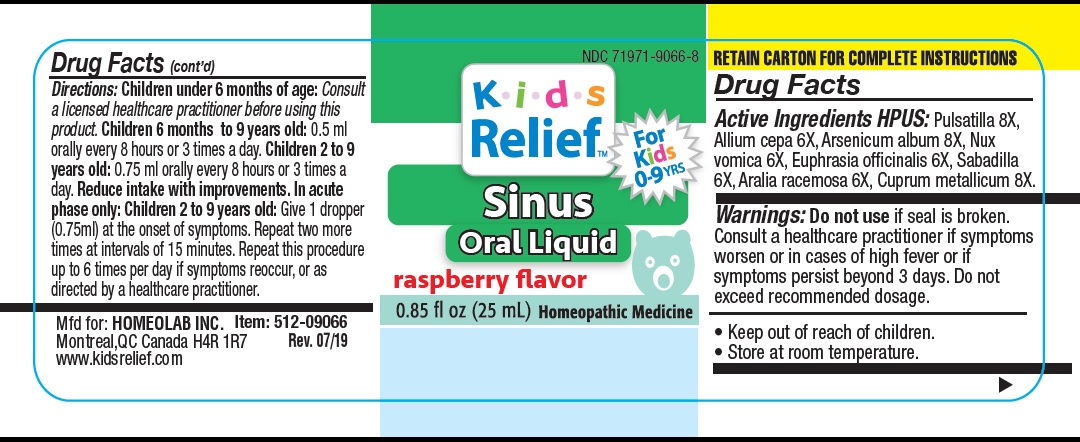 DRUG LABEL: Kids Relief
NDC: 71971-9066 | Form: LIQUID
Manufacturer: Homeolab International (Canada) inc
Category: homeopathic | Type: HUMAN OTC DRUG LABEL
Date: 20190725

ACTIVE INGREDIENTS: ANEMONE PULSATILLA 8 [hp_X]/25 mL; ONION 6 [hp_X]/25 mL; ARSENIC TRIOXIDE 8 [hp_X]/25 mL; STRYCHNOS NUX-VOMICA SEED 6 [hp_X]/25 mL; EUPHRASIA STRICTA 6 [hp_X]/25 mL; SCHOENOCAULON OFFICINALE SEED 6 [hp_X]/25 mL; ARALIA RACEMOSA ROOT 6 [hp_X]/25 mL; COPPER 8 [hp_X]/25 mL
INACTIVE INGREDIENTS: WATER; SORBITOL; SODIUM BENZOATE; POTASSIUM SORBATE; CITRIC ACID ACETATE; RASPBERRY

Active Ingredients HPUS:

Pulsatilla 8X

(Wind flower)

Allium cepa 6X (Onion)

Arsenicum album 8X

(Arsenous oxide)

Nux Vomica 6X

(Poison nut)

Euphrasia officinalis 6X

(Eyebright)

Sabadilla 6X (Cevadilla)

Aralia racemosa 6X (Spikenard)

Cuprum metallicum 8X

(Metallic copper)

Purpose

Sinus symptoms, sneezing, nasal congestion, runny nose, itchy eyes, nose and throat, watery eyes headache, throat irritation.

The letters 'HPUS' indicate that the components in this product are officially monographed in the Homoeopathic Pharmacopoeia of the United States.

*Claims based on traditional homeopathic practice, not accepted medical evidence. Not FDA evaluated

Uses

This homeopathic medicine is made from a combination of ingredients traditionally used to help relieve indispositions caused by sinus symptoms*:

• sneezing
• nasal congestion
• runny nose
• itchy eyes, nose and throat
• watery eyes
• headache
• throat irritation

Warnings

Do not use if seal is broken or missing.

Stop use and ask a doctor in cases of high fever or if symptoms worsen or persist for more than 3 days.

Keep out of reach of children.

Directions

Children under 6 months of age: Consult a licensed healthcare practitioner before using this product.

Children 6 months to 9 years old: 0.5 ml orally every 8 hours or 3 times a day.

Children 2 to 9 years old: 0.75 ml orally every 8 hours or 3 times a day.

Reduce intake with improvements.

In acute phase only:

Children 2 to 9 years old; Give 1 dropper (0.75ml) at the onset of symptoms. Repeat two more times at intervals of 15 minutes.

Repeat this procedure up to 6 times per day if symptoms reoccur, or as directed by a healthcare practitioner.

Not to be taken with meals

Other information

•Store at room temperature

Inactive Ingredients

Purified water, sorbitol, sodium benzoate, potassium sorbate, citric acid, raspberry flavour.